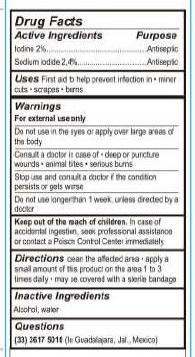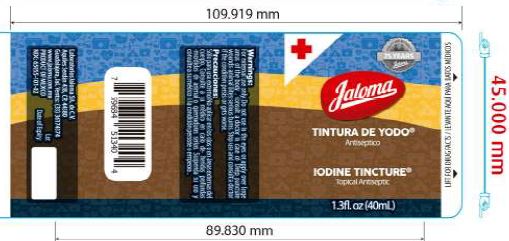 DRUG LABEL: Iodine Tincture
NDC: 65055-101 | Form: TINCTURE
Manufacturer: Laboratorios Jaloma, S.A. de C.V.
Category: otc | Type: HUMAN OTC DRUG LABEL
Date: 20231109

ACTIVE INGREDIENTS: IODINE 2 g/100 mL; SODIUM IODIDE 2.4 g/100 mL
INACTIVE INGREDIENTS: WATER; ALCOHOL

Iodine Tincture Topical Antiseptic

Active Ingredients

Iodine 2.0%

Sodium Iodide 2.4%

Purpose

Antiseptic

Antiseptic

Uses

First aid to help prevent infection in *minor cuts *scrapes *burns

Warnings For external use only

Do not use in the eyes or apply over large areas of

the body

Do not use longer than 1 week, unless directed by a

doctor

ASK DOCTOR

Consult a doctor in case of * deep or puncture

wounds * animal bites * serious burns

STOP USE

if the condition Stop use and consult a doctor

persists or gets worse

KEEP OUT OF REACH OF CHILDREN

In case of Keep out of the reach of children.

accidental ingestion, seek professional assistance

or contact a Poison Control Center immediately.

DOSAGE AND ADMINISTRATION

clean the affected area * apply a Directions

small amount of this product on the area 1 to 3

times daily * may be covered with a sterile bandage

Inactive Ingredients

alcohol, water

Questions

(33) 3617 5010 (In Guadalajara, Jal. Mexico)